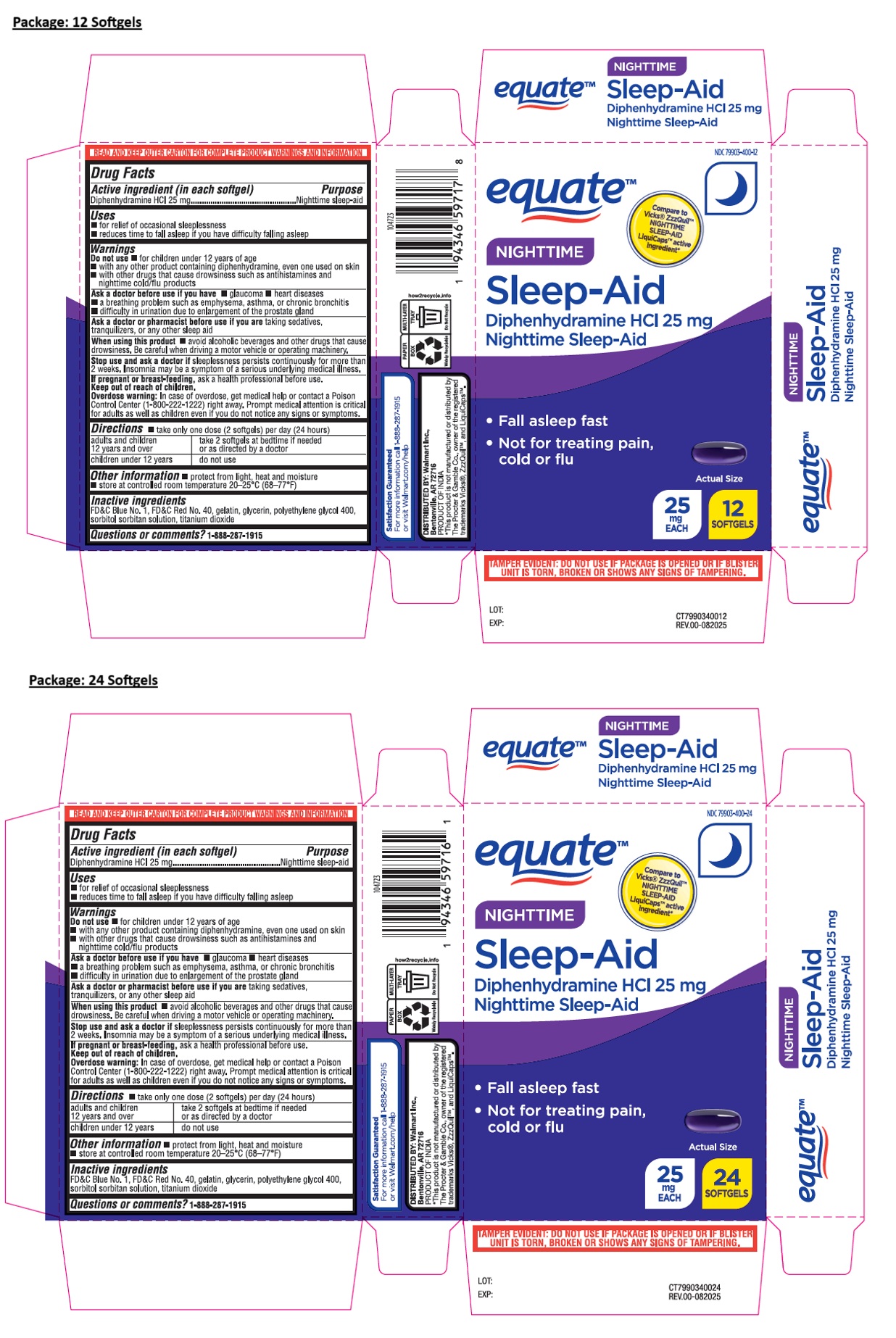 DRUG LABEL: equate NIGHTTIME Sleep-Aid
NDC: 79903-400 | Form: CAPSULE, LIQUID FILLED
Manufacturer: WALMART INC.
Category: otc | Type: HUMAN OTC DRUG LABEL
Date: 20251021

ACTIVE INGREDIENTS: DIPHENHYDRAMINE HYDROCHLORIDE 25 mg/1 1
INACTIVE INGREDIENTS: FD&C BLUE NO. 1; FD&C RED NO. 40; GELATIN, UNSPECIFIED; GLYCERIN; POLYETHYLENE GLYCOL 400; SORBITOL; SORBITAN; TITANIUM DIOXIDE

equate™ NIGHTTIME Sleep-Aid

Active ingredient (in each softgel)

Diphenhydramine HCl 25 mg

Purpose

Nighttime sleep-aid

Uses

• for relief of occasional sleeplessness
• reduces time to fall asleep if you have difficulty falling asleep

Warnings

Do not use • for children under 12 years of age
• with any other product containing diphenhydramine, even one used on skin
• with other drugs that cause drowsiness such as antihistamines and nighttime cold/flu products

Ask a doctor before use if you have • glaucoma • heart diseases
• a breathing problem such as emphysema, asthma, or chronic bronchitis
• difficulty in urination due to enlargement of the prostate gland

Ask a doctor or pharmacist before use if you are taking sedatives, tranquilizers, or any other sleep aid

When using this product • avoid alcoholic beverages and other drugs that cause drowsiness. Be careful when driving a motor vehicle or operating machinery.

Stop use and ask a doctor if sleeplessness persists continuously for more than 2 weeks. Insomnia may be a symptom of a serious underlying medical illness.

If pregnant or breast-feeding, ask a health professional before use.

Keep out of reach of children.
Overdose warning: In case of overdose, get medical help or contact a Poison Control Center (1-800-222-1222) right away. Prompt medical attention is critical for adults as well as children even if you do not notice any signs or symptoms.

Directions

• take only one dose (2 softgels) per day (24 hours)

adults and children 12 years and over | take 2 softgels at bedtime if needed or as directed by a doctor
children under 12 years | do not use

Other information

• protect from light, heat and moisture
• store at controlled room temperature 20-25°C (68-77°F)

Inactive ingredients

FD&C Blue No. 1, FD&C Red No. 40, gelatin, glycerin, polyethylene glycol 400, sorbitol sorbitan solution, titanium dioxide

Questions or comments?

1-888-287-1915

Compare to Vicks® ZzzQuil™ NIGHTTIME SLEEP-AID LiquiCaps™ active ingredient*

• Fall asleep fast
• Not for treating pain, cold or flu

READ AND KEEP OUTER CARTON FOR COMPLETE PRODUCT WARNINGS AND INFORMATION

Satisfaction GuaranteedFor more information call 1-888-287-1915 or visit Walmart.com/help

DISTRIBUTED BY: Walmart Inc.,
Bentonville, AR 72716

PRODUCT OF INDIA

*This product is not manufactured or distributed by The Procter & Gamble Co., owner of the registered trademarks Vicks®, ZzzQuil™, and LiquiCaps™.

TAMPER EVIDENT: DO NOT USE IF PACKAGE IS OPENED OR IF BLISTER UNIT IS TORN, BROKEN OR SHOWS ANY SIGNS OF TAMPERING.